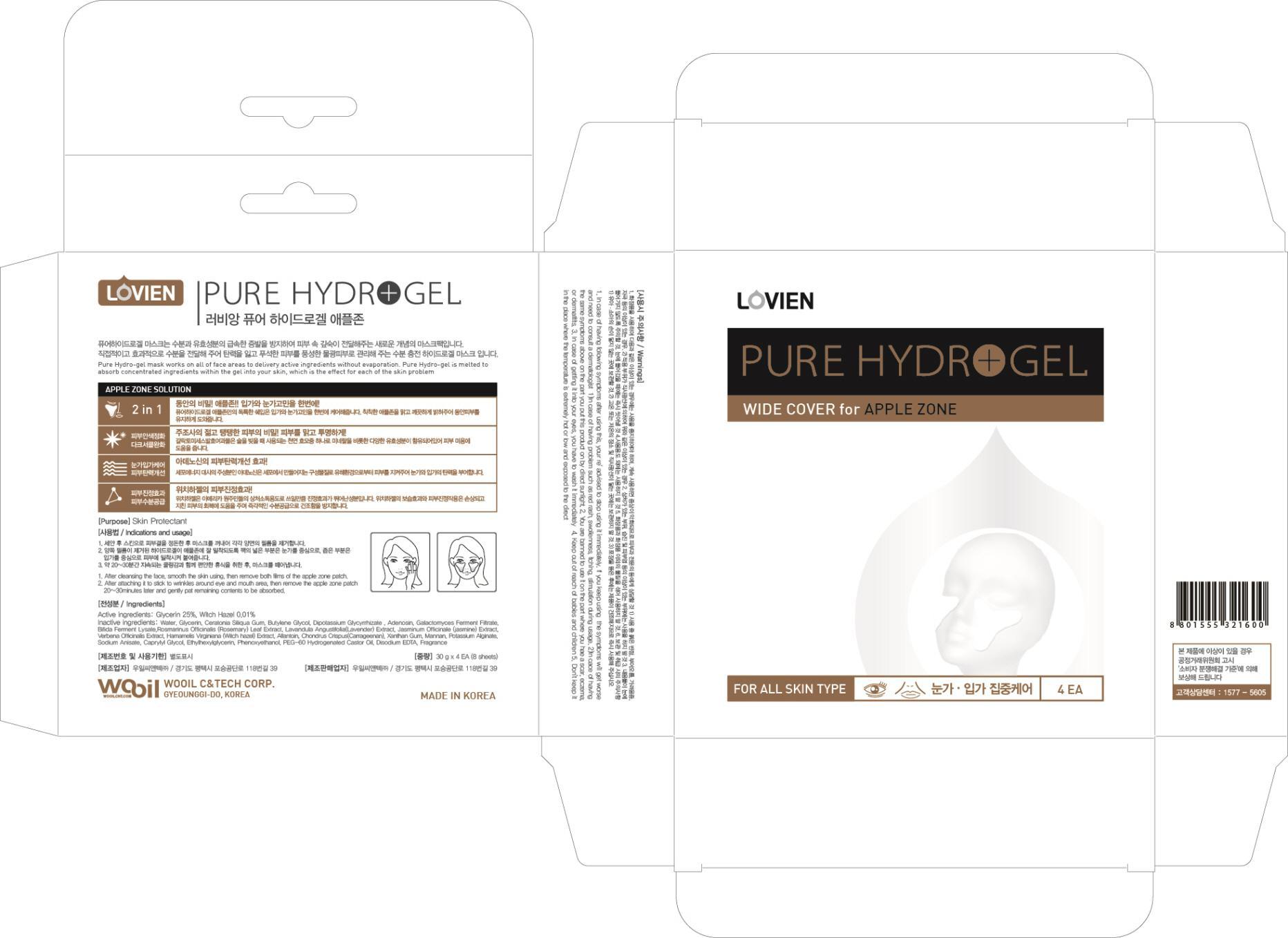 DRUG LABEL: PURE HYDROGEL APPLE ZONE
NDC: 58474-020 | Form: PATCH
Manufacturer: WOOIL C&TECH.CORP
Category: otc | Type: HUMAN OTC DRUG LABEL
Date: 20130523

ACTIVE INGREDIENTS: Glycerin 7.5 g/30 g
INACTIVE INGREDIENTS: Water; Butylene Glycol; Adenosine

ACTIVE INGREDIENT

Active ingredients: Glycerin 25%, Witch Hazel 0.01%

INACTIVE INGREDIENT

Inactive ingredients:
Water, Ceratonia Siliqua Gum, Butylene Glycol, Dipotassium Glycyrrhizate, Adenosine, Galactomyces Ferment Filtrate, Bifida Ferment Lysate,Rosmarinus Officinalis (Rosemary) Leaf Extract, Lavandula Angustifolia(Lavender) Extract, Jasminum Officinale (jasmine) Extract,
Verbena Officinalis Extract, Allantoin, Chondrus Crispus(Carrageenan), Xanthan Gum, Mannan, Potassium Alginate, Sodium Anisate, Caprylyl Glycol, Ethylhexylglycerin, Phenoxyethanol, PEG-60 Hydrogenated Castor Oil, Disodium EDTA, Fragrance

PURPOSE

Purpose: Skin Protectant

WARNINGS

1. In case of having following symptoms after using this, your re' advised to stop using it immediately. If you keep using the symptoms will get worse and need to consult a dermatologist.
1)In case of having problem such as red rash, swollenness, itching, stimulation during usage.
2)In cace of having the same symptoms above on the part you put this product on by direct sunlight.
2. You are banned to use it on the part where you hae a scar, eczema, or dermatitits.
3. In case of getting it into your eyes, you have to wash it immediately
4. Keep out of reach of babies and children
5. Don't keep it in the place where the temperature is extremely hot or low and exposed to the direct

KEEP OUT OF REACH OF CHILDREN

Keep out of reach of babies and children

INDICATIONS AND USAGE

1. After cleansing the face, smooth the skin using a toner, then remove film on both sides of hydro-gel mask.
2. Apply and gently press the upper mask on your face considering the position of eyes, lower mask on your face considering the position of mouth.
3. Rest comfortably for 20-30 minutes and removed the mask.

DOSAGE AND ADMINISTRATION

1. After cleansing the face, smooth the skin using a toner, then remove film on both sides of hydro-gel mask.
2. Apply and gently press the upper mask on your face considering the position of eyes, lower mask on your face considering the position of mouth.
3. Rest comfortably for 20-30 minutes and removed the mask.